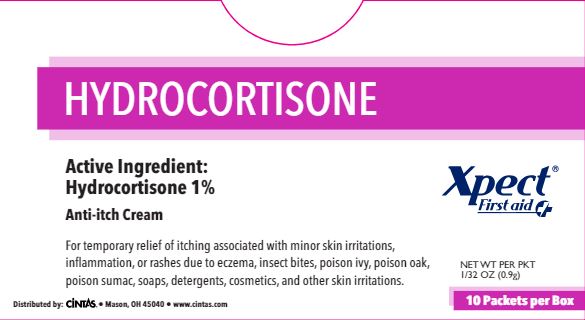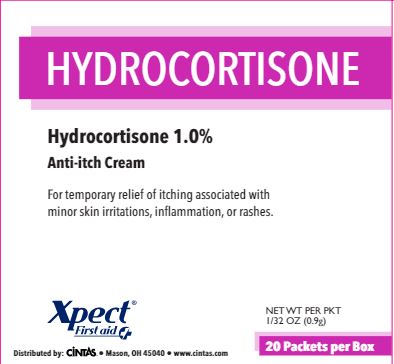 DRUG LABEL: Xpect Hydrocortisone
NDC: 42961-237 | Form: CREAM
Manufacturer: Cintas Corporation
Category: otc | Type: HUMAN OTC DRUG LABEL
Date: 20250926

ACTIVE INGREDIENTS: HYDROCORTISONE 0.01 g/1 g
INACTIVE INGREDIENTS: METHYLPARABEN; MINERAL OIL; PARAFFIN; PETROLATUM; PROPYLPARABEN; WATER; ALCOHOL; CETOSTEARYL ALCOHOL; POLYSORBATE 60; PEG-150 DISTEARATE; STEARETH-20

Xpect Hydrocortisone

Active ingredients (in each gram)

Hydrocortisone 1%

Purpose

Anti-itch cream

Uses

- for the temporary relief of itching associated with minor skin irritations, inflammation and rashes due to eczema, insect bites, poison ivy, poison oak, poison sumac, soaps, detergents, cosmetics, jewelry, seborrheic dermatitis, psoriasis, and scrapes
- other uses of product should be only under the advice and supervision of a doctor

Warnings

For external use only.

Do not use

- for the treatment of diaper rash
- in eyes
- for feminine itching

Stop use and ask a doctor if

- condition worsens or lasts more than 7 days, or clears up and ocurs again within a few days
- you begin use of any other Hydrocortisone product unless you have consulted a doctor
- if bleeding occurs

Keep out of reach of children. If swallowed, get medical help or contact a Poison Control Center right away.

Directions

- for adults and children 2 years of age and older: apply to affected area 3 to 4 times daily
- children under 12 years of age: for external anal itching, consult a doctor
- children under 2: do not use, consult a doctor
- adults for external anal itching when practical, cleanse the affected area with mild soap and warm water and rinse thoroughly or by patting or blotting with an appropriate cleansing pad
- gently dry by patting or blotting with toilet tissue or a soft cloth before application of this product

Other Information

- clean the affected area
- store at room temperature (do not freeze)
- do not use any opened or torn packets

Inactive ingredients

cetyl alcohol*, citric acid*, diazolidinyl urea*, edetate disodium*, emulsifying wax*, ethanol*, glycerin*, glyceryl monostearate*, methylparaben, mineral oil, paraffin*, petrolatum*, polyethylene glycol*, propylene glycol*, propylparaben, stearic acid*, trolamine*, water, white wax*
*may contain ingredient

Questions?

1-877-973-2811 M-F 8 am - 5 pm

Principal Display Panel 42961-235-02

HYDROCORTISONE

Active Ingredient:

Hydrocortisone 1%

Anti-itch cream

For temporary relief of itching associated with minor skin irritations, inflammation, or rashes due to eczema, insect bites, poison ivy, poison oak, poison sumac, soaps, detergents, cosmetics, and other skin irritations.

Distributed by: Cintas • Mason, OH 45040 • www.cintas.com

Xpect® First aid

NET WT PER PKT 1/32 OZ (0.9g)

10 Packets per Box

Principal Display Panel 42961-235-03

HYDROCORTISONE

Hydrocortisone 1%

Anti-itch cream

For temporary relief of itching associated with minor skin irritations, inflammation, or rashes.

Xpect® First aid

Distributed by: Cintas • Mason, OH 45040 • www.cintas.com

NET WT PER PKT 1/32 OZ (0.9g)

20 Packets per Box